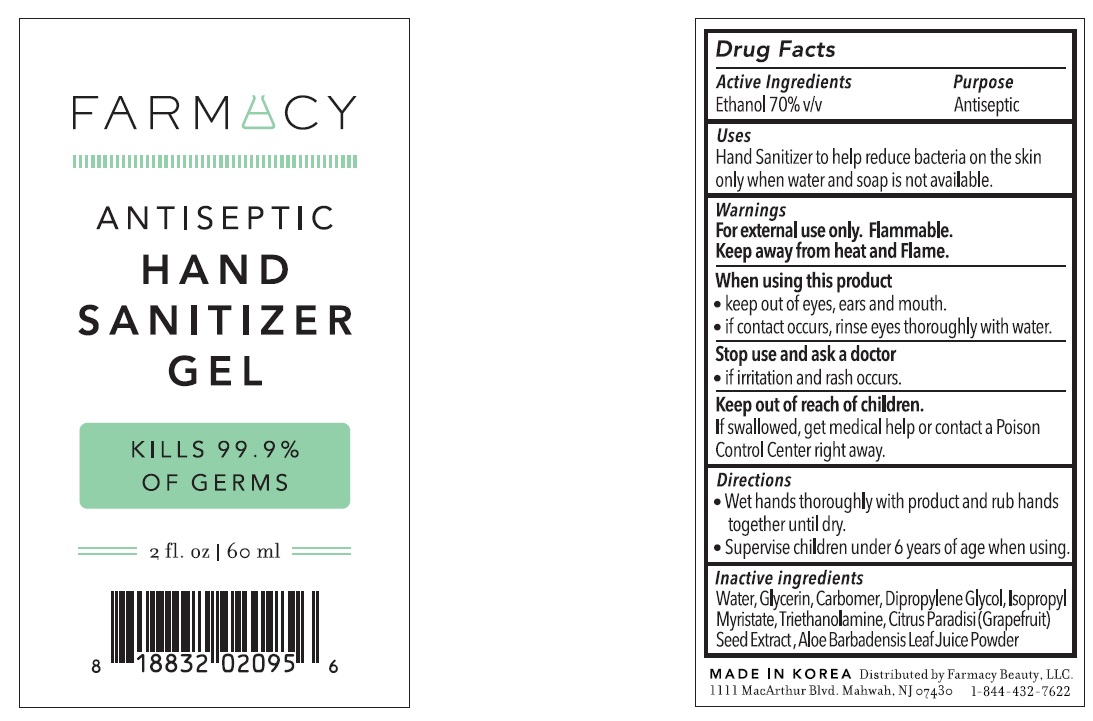 DRUG LABEL: FARMACY ANTISEPTIC HAND SANITIZER
NDC: 73819-0005 | Form: GEL
Manufacturer: GuStar Co Ltd
Category: otc | Type: HUMAN OTC DRUG LABEL
Date: 20200418

ACTIVE INGREDIENTS: ALCOHOL 42 g/60 mL
INACTIVE INGREDIENTS: Water; Glycerin; CARBOMER HOMOPOLYMER, UNSPECIFIED TYPE; Dipropylene Glycol; ISOPROPYL MYRISTATE; Trolamine; CITRUS PARADISI SEED; ALOE VERA LEAF

ACTIVE INGREDIENT

Active ingredients: ETHANOL 70% v/v

INACTIVE INGREDIENT

Inactive ingredients

Water, Glycerin, Carbomer, Dipropylene Glycol, Isopropylene Myristate, Triethanolamine, Citrus Paradisi (Grapefruit) Seed Extract, Aloe Barbadensis Leaf Juice Powder

PURPOSE

Purpose: ANTISEPTIC

WARNINGS

For external use only. Flammable. Keep away from heat and flame
--------------------------------------------------------------------------------------------------------
When using this product
keep out of eyes, ears, and mouth.
if contact occurs, rinse eyes thoroughly with water
--------------------------------------------------------------------------------------------------------
Stop use and ask a doctor
if irritation or rash occurs.

Keep out of reach of children. If swallowed, get medical help or contact a Poison Control Center right away.

Uses

Hand sanitizer to help reduce bacteria on skin only when water and soap is not available

Directions

• Wet hands throughly with product and rub hands together until dry
• Supervise children under 6 years of age when using.